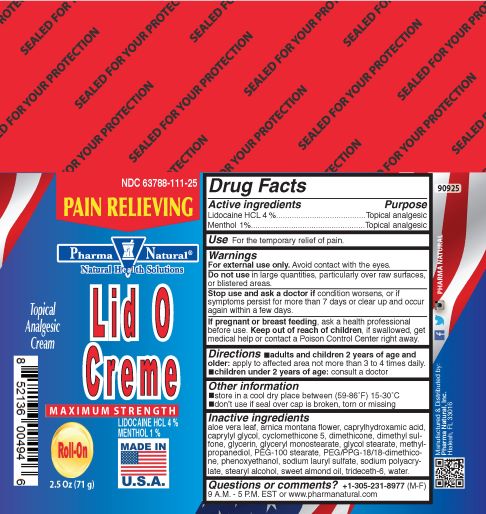 DRUG LABEL: LID O CREME ROLL ON
NDC: 63788-111 | Form: CREAM
Manufacturer: Pharma Natural, Inc.
Category: otc | Type: HUMAN OTC DRUG LABEL
Date: 20180831

ACTIVE INGREDIENTS: MENTHOL 1 g/100 g; LIDOCAINE HYDROCHLORIDE 4 g/100 g
INACTIVE INGREDIENTS: ARNICA MONTANA FLOWER; CAPRYLHYDROXAMIC ACID; SODIUM LAURYL SULFATE; SODIUM POLYACRYLATE (8000 MW); TRIDECETH-6; WATER; ALOE VERA LEAF; ALPHA-TOCOPHEROL; DIMETHYL SULFONE; GLYCERIN; GLYCERYL MONOSTEARATE; DIMETHICONE; GLYCOL STEARATE; METHYLPROPANEDIOL; ALMOND OIL; PHENOXYETHANOL; PEG-100 STEARATE; PEG/PPG-18/18 DIMETHICONE; CAPRYLYL GLYCOL; CYCLOMETHICONE 5; STEARYL ALCOHOL

LID O CREME

Active ingredients and Purpose

Active ingredients | Purpose
Lidocaine HCL 4%............................ | Topical analgesic
Menthol 1%....................................... | Topical analgesic

Use

For the temporary relief of pain.

Warnings

For external use only. Avoid contact with the eyes.

Do not use

in large quantities, particularly over raw surfaces, or blistered areas.

Stop use and ask a doctor if

condition worsens, or if symptoms persist for more than 7 days or clear up and occur again within a few days.

If pregnant or breast feeding,

ask a health professional before use.

Keep out of reach of children.

If swallowed, get medical help, or contact a Poison Control Center immediately.

Directions

▪adults and children 2 years of age and older: apply to affected area not more than 3 to 4 times daily

▪children under 2 years of age: consult a doctor

Other information

▪ store in a cool dry place between (59-86°F)15-30°C

▪ don’t use if seal over cap is broken, torn, or missing

Inactive ingredients

aloe vera leaf, alpha-tocopherol, arnica montana flower, caprylhydroxamic acid, caprylyl glycol, cyclomethicone 5, dimethicone, dimethyl sulfone, glycerin, glyceryl monostearate, glycol stearate, methylpropanediol, PEG-100 stearate, PEG/PPG-18/18-dimethicone, phenoxyethanol, sodium lauryl sulfate, sodium polyacrylate, stearyl alcohol, sweet almond oil, trideceth-6, water

Questions or comments?

+1-305-231-8977 (M-F) 9 A.M. - 5 P.M. EST or www.pharmanatural.com

Manufactured & Distributed by:

Pharma Natural, Inc.

Hialeah, FL 33016

Principal Display Panel

PAIN RELIEVING

Pharma Natural

Natural Health Solutions

Lid O Creme

Maximum Strength

Topical Analgesic Cream

Roll-On

LIDOCAINE HCL 4%

MENTHOL 1%

2.5 oz. (71 g)